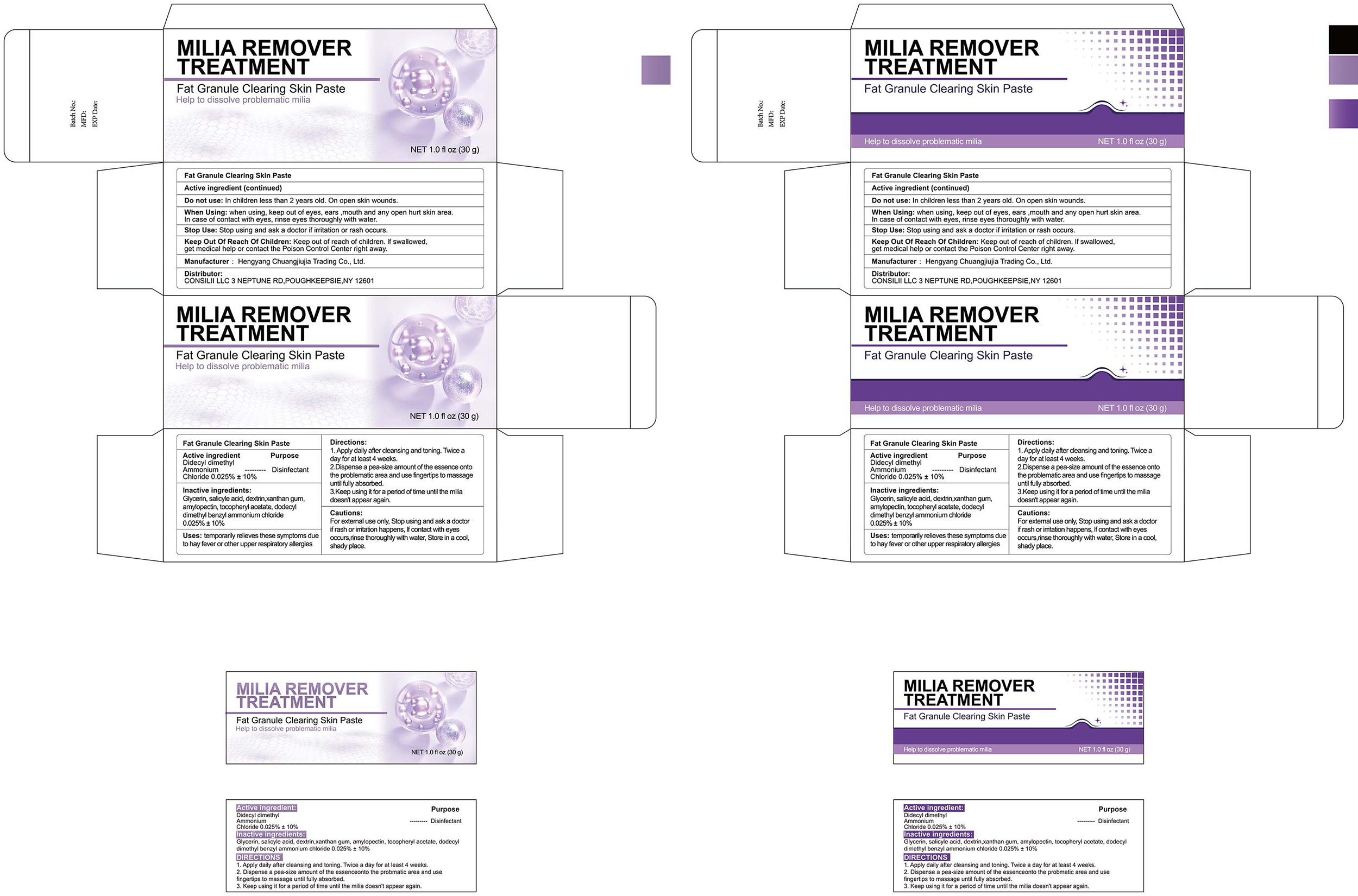 DRUG LABEL: Milia remover treatment
NDC: 84735-009 | Form: CREAM
Manufacturer: Hengyang Chuangjiujia Trading Co., Ltd.
Category: otc | Type: HUMAN OTC DRUG LABEL
Date: 20250516

ACTIVE INGREDIENTS: DIDECYLDIMONIUM 0.025 g/100 g
INACTIVE INGREDIENTS: SALICYLIC ACID; AMYLOPECTIN, UNSPECIFIED SOURCE; XANTHAN GUM; .ALPHA.-TOCOPHEROL ACETATE; ICODEXTRIN; BENZALKONIUM; GLYCERIN

84735-009 Milia remover treatment

ACTIVE INGREDIENT

Dioctyl Dimethyl Ammonium Chloride 0.025%

PURPOSE

Disinfectant

INDICATIONS AND USAGE

Uses: temporarily relieves these symptoms dueto hay fever or other upper respiratory allergies

WARNINGS

For extemal use only.

Do not use: In children less than 2 years old. On open skin wounds.

WHEN USING

When Using: when using, keep out of eyes, ears ,mouth and any open hurt skin area. In case of contact with eyes, rinse eyes thoroughly with water.

Stop Use: Stop using and ask a doctor if irritation or rash occurs.

Keep Out Of Reach Of Children: Keep out of reach of children. if swallowed
get medical help or contact the Poison Control Center right away.

DOSAGE AND ADMINISTRATION

1.Apply daily after deansing and toning. Twice aday for at least 4 weeks.
2.Dispense a pea-size amount of the essence ontothe problematic area and use fingertips to massageuntil fully absorbed
3.Keep using it for a perod of time until the miliadoesn't appear again.

INACTIVE INGREDIENT

Glycerin
Salicylic Acid
Dextrin
Xanthan Gum
Amylopectin
Tocopheryl Acetate
Dodecyl Dimethyl Benzyl Ammonium Chloride